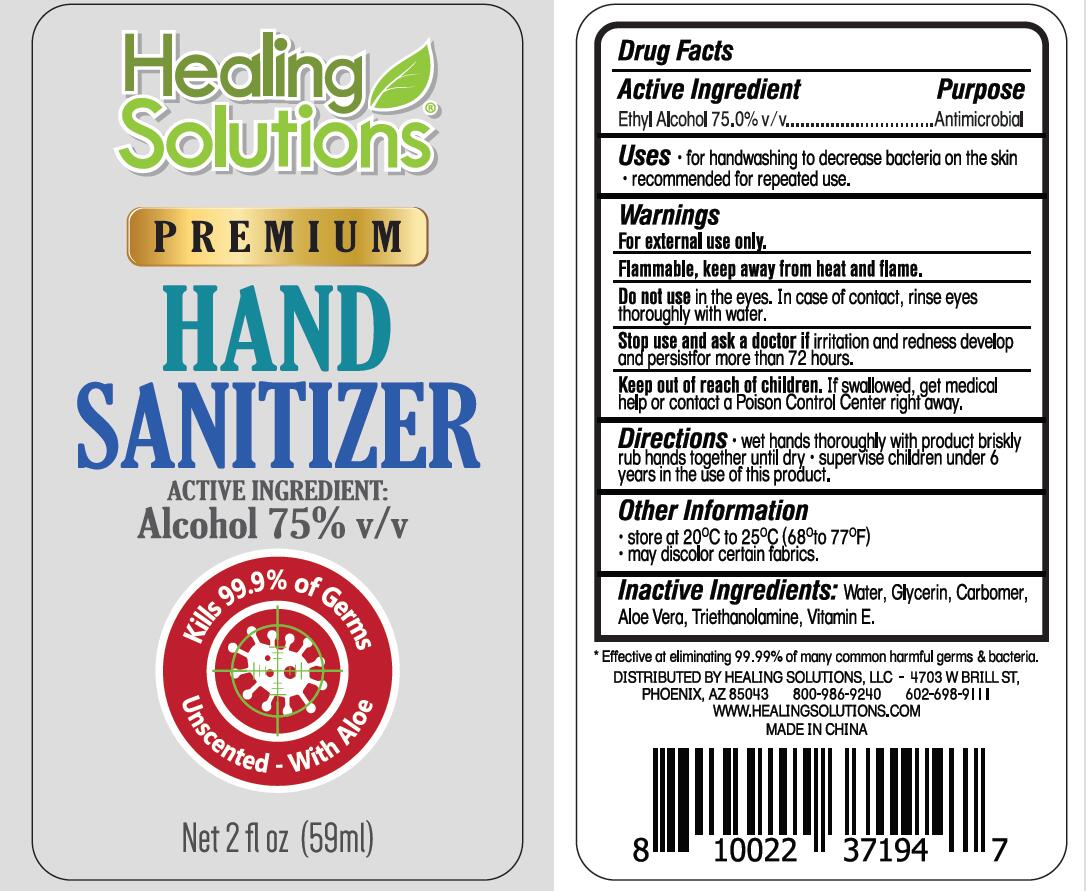 DRUG LABEL: Hand Sanitizer
NDC: 58503-801 | Form: GEL
Manufacturer: China Ningbo Shangge Cosmetic Technology Corp.
Category: otc | Type: HUMAN OTC DRUG LABEL
Date: 20200609

ACTIVE INGREDIENTS: ALCOHOL 75 mL/100 mL
INACTIVE INGREDIENTS: ALOE VERA LEAF; GLYCERIN; CARBOMER HOMOPOLYMER, UNSPECIFIED TYPE; WATER; TROLAMINE; .ALPHA.-TOCOPHEROL SUCCINATE, D-

Hand Sanitizer

Active Ingredient(s)

Ethyl Alcohol 75% v/v.

Purpose

Antimicrobial

Use

for handwashing to decrease bacteria on the skin

recommended for repeated use

Warnings

For external use only
Flammable, keep away from heat and flame.

Do not use in the eyes In case of contact rinse eyes thoroughly with wafer

WHEN USING

/

Stop use, and ask a doctor if irritation and redness develop and persistfor more than 72 hours.

Keep out of reach of children. If swallowed. get medical help or contact a Poison Control Center right away.

Directions

wet hands thoroughly with product briskly rub hands together until dry
supervise children under 6 years in the use of this product

Other information

store at 20°C to 25°C(68° to 77°F)
may discolor certain fabrics

Inactive ingredients

Water, Glycerin, Carbomer, Aloe Vera, Trithanolamine, Vitamine E